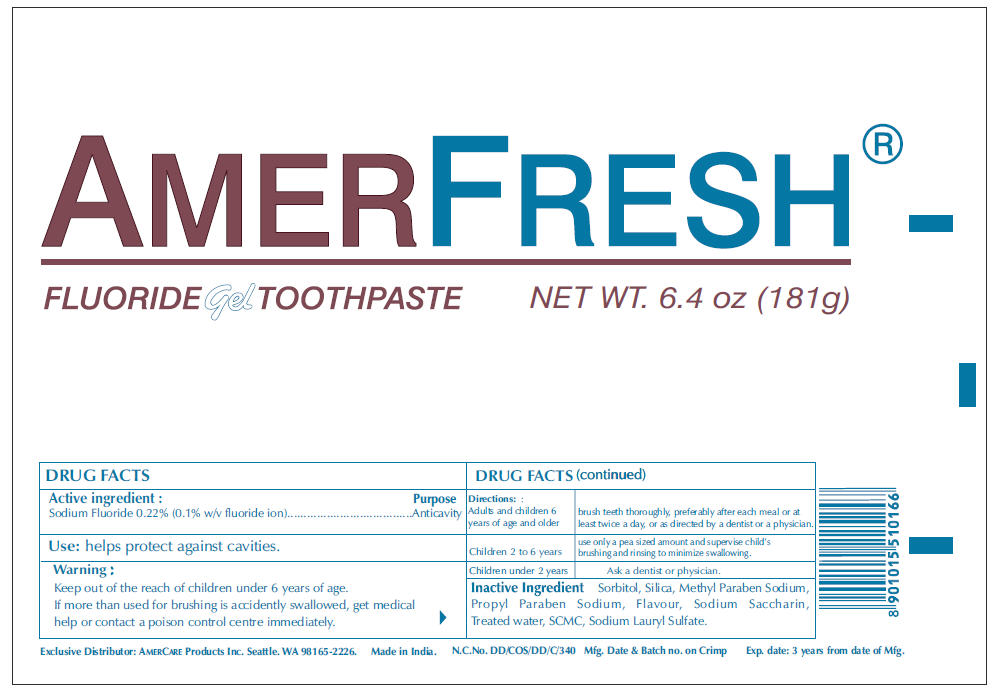 DRUG LABEL: Amerfresh Clear
NDC: 51460-5010 | Form: PASTE, DENTIFRICE
Manufacturer: Amercare Products Inc
Category: otc | Type: HUMAN OTC DRUG LABEL
Date: 20110316

ACTIVE INGREDIENTS: Sodium Fluoride 0.22 g/100 g
INACTIVE INGREDIENTS: Sorbitol 64 g/100 g; Water; Silicon Dioxide; Sodium Lauryl Sulfate; Carboxymethylcellulose Sodium; Saccharin Sodium; Methylparaben Sodium; Propylparaben Sodium

AMERFRESH®

FLUORIDE gel TOOTHPASTE

Active ingredient

Sodium Fluoride 0.22% (0.1% w/v fluoride ion)

Purpose

Anticavity

Use

helps protect against cavities.

Warning

KEEP OUT OF REACH OF CHILDREN

Keep out of the reach of children under 6 years of age.
If more than used for brushing is accidently swallowed, get medical help or contact a poison control centre immediately.

Directions

Adults and children 6 years of age and older | brush teeth thoroughly, preferably after each meal or at least twice a day, or as directed by a dentist or a physician.
Children 2 to 6 years | use only a pea sized amount and supervise child's brushing and rinsing to minimize swallowing.
Children under 2 years | Ask a dentist or physician.

Inactive Ingredient

Sorbitol, Silica, Methyl Paraben Sodium, Propyl Paraben Sodium, Flavour, Sodium Saccharin, Treated water, SCMC, Sodium Lauryl Sulfate.

Exclusive Distributor: AMERCARE Products Inc. Seattle. WA 98165-2226.

PRINCIPAL DISPLAY PANEL - 181 g Carton Label

AMERFRESH®

FLUORIDE gel TOOTHPASTE

NET WT. 6.4 oz (181g)